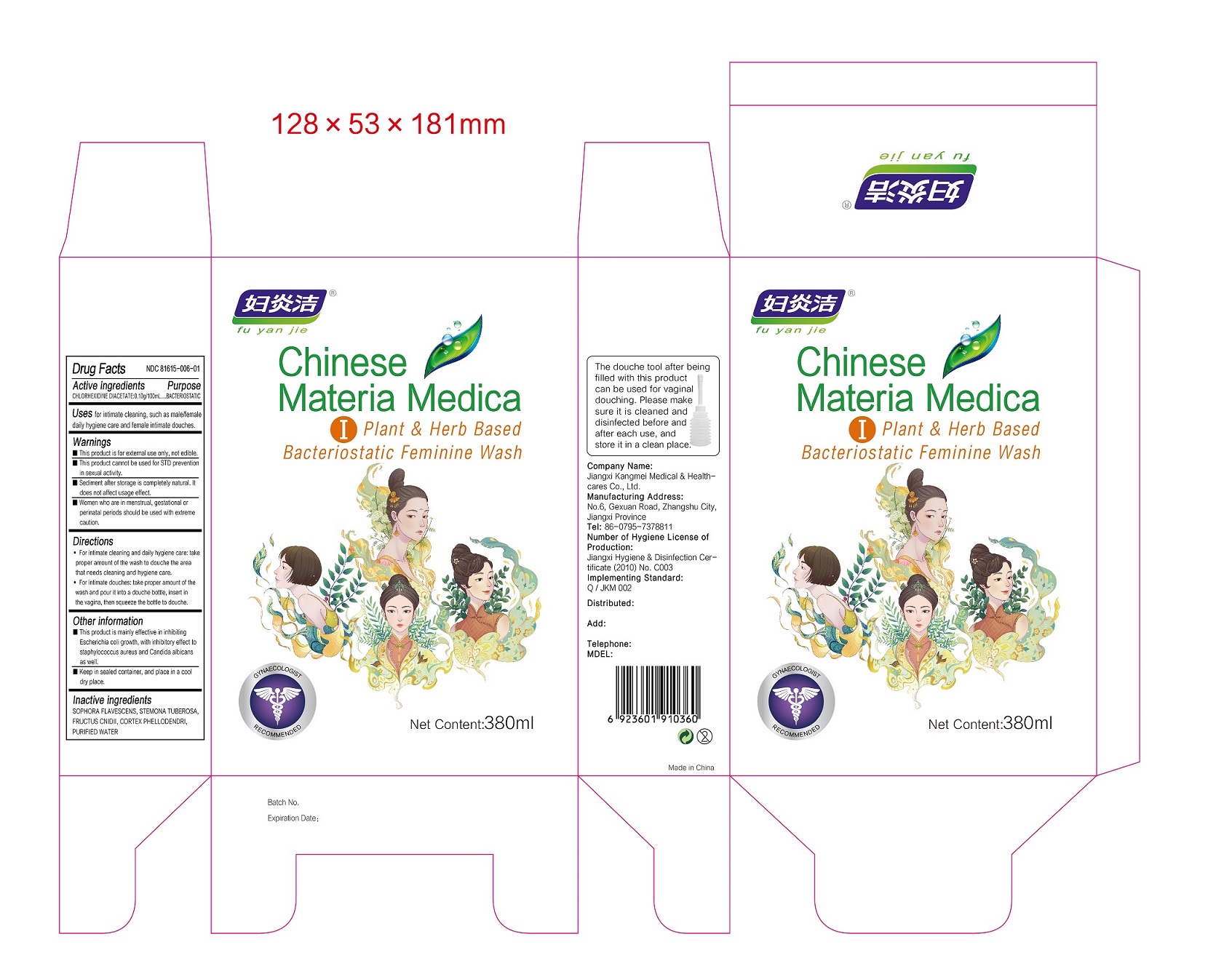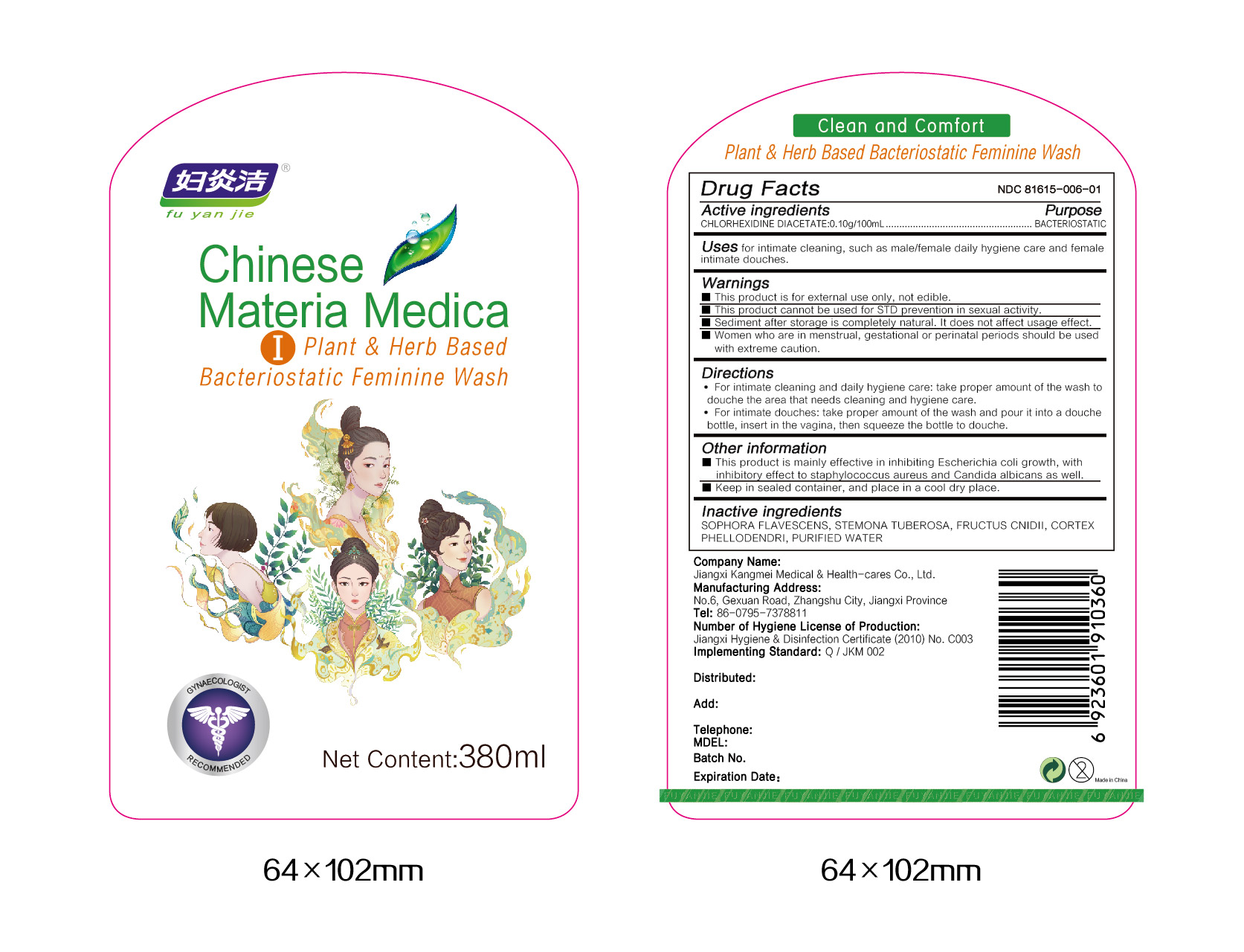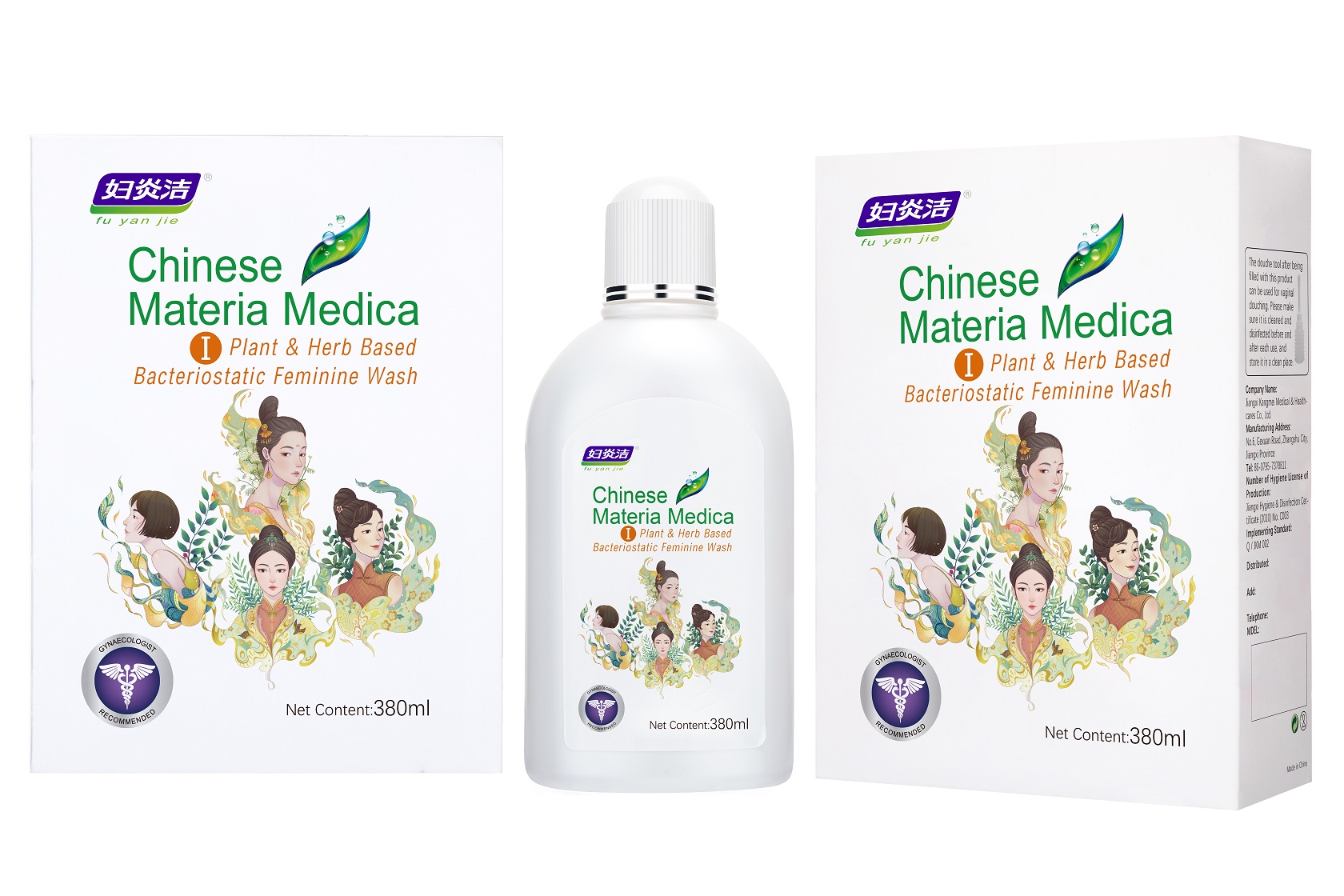 DRUG LABEL: PLANT HERB BASED BACTERIOSTATIC FEMININE WASH
NDC: 81615-006 | Form: LIQUID
Manufacturer: Jiangxi Renhetang pharmaceutical chain Co., Ltd.
Category: otc | Type: HUMAN OTC DRUG LABEL
Date: 20210420

ACTIVE INGREDIENTS: CHLORHEXIDINE ACETATE 0.1 g/100 mL
INACTIVE INGREDIENTS: OSTHOL; SOPHORA FLAVESCENS ROOT; STEMONA TUBEROSA ROOT; WATER; PHELLODENDRON CHINENSE WHOLE

PLANT & HERB BASED BACTERIOSTATIC FEMININE WASH

PLANT & HERB BASED BACTERIOSTATIC FEMININE WASH

Active Ingredient(s)

CHLORHEXIDINE DIACETATE 0.10g/100mL

Purpose

BACTERIOSTATIC

Use

Uses for intimate cleaning, such as male/female daily hygiene care and female intimate douches.

Warnings

This product is for external use only, not edible.

This product cannot be used for STD prevention in sexual activity.

Sediment after storage is completely natural. It does not affect usage effect.

Women who are in menstrual, gestational or perinatal periods should be used with extreme caution.

When using this product keep out of eyes, ears, and mouth. In case of contact with eyes, rinse eyes thoroughly with water.
Stop use and ask a doctor if irritation or rash occurs. These may be signs of a serious condition.
Keep out of reach of children. If swallowed, get medical help or contact a Poison Control Center right away.

Stop use and ask a doctor if irritation or rash occurs. These may be signs of a serious condition.

Keep out of reach of children. If swallowed, get medical help or contact a Poison Control Center right away.

Directions

1. For intimate cleaning and daily hygiene care: take proper amount of the wash to douche the area that needs cleaning and hygiene care.
2. For intimate douches: take proper amount of the wash and pour it into a douche bottle, insert in the vagina, then squeeze the bottle to douche

Other information

This product is mainly effective in inhibiting Escherichia coli growth, with inhibitory effect to staphylococcus aureus and Candida albicans as well.

Keep in sealed container, and place in a cool dry place.

Inactive ingredients

SOPHORA FLAVESCENS
STEMONA TUBEROSA
FRUCTUS CNIDII
CORTEX PHELLODENDRI
PURIFIED WATER